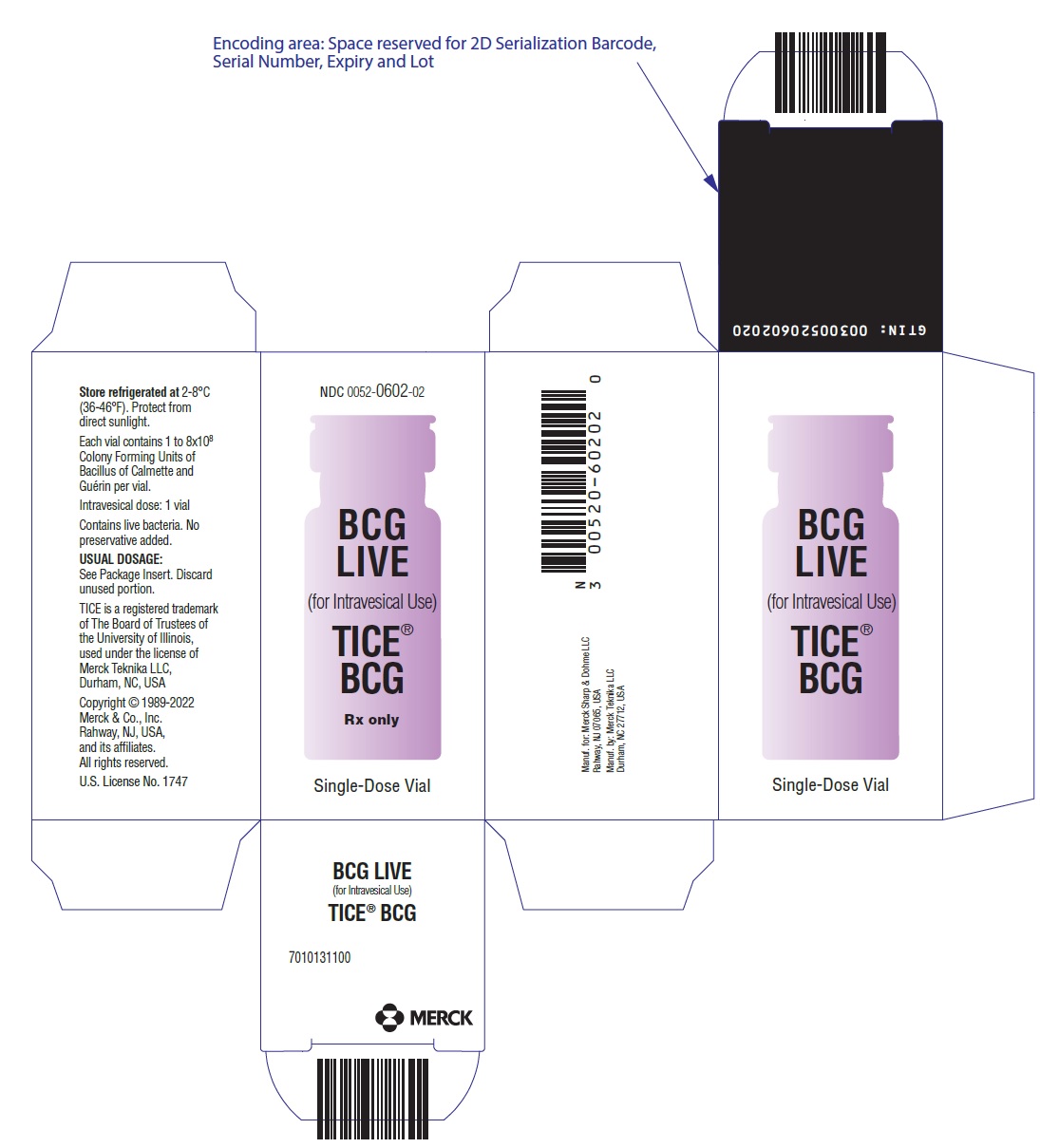 DRUG LABEL: TICE BCG
NDC: 0052-0602 | Form: POWDER, FOR SUSPENSION
Manufacturer: Merck Sharp & Dohme LLC
Category: prescription | Type: HUMAN PRESCRIPTION DRUG LABEL
Date: 20250828

ACTIVE INGREDIENTS: BACILLUS CALMETTE-GUERIN SUBSTRAIN TICE LIVE ANTIGEN 50 mg/50 mL
INACTIVE INGREDIENTS: GLYCERIN; ASPARAGINE; CITRIC ACID MONOHYDRATE; POTASSIUM PHOSPHATE, UNSPECIFIED FORM; MAGNESIUM SULFATE, UNSPECIFIED FORM; LACTOSE, UNSPECIFIED FORM; FERRIC AMMONIUM CITRATE

TICE® BCG
BCG Live
For Intravesical Use

WARNING

TICE® BCG contains live, attenuated mycobacteria. Because of the potential risk for transmission, prepare, handle, and dispose of TICE® BCG as a biohazard material (see PRECAUTIONS and DOSAGE AND ADMINISTRATION sections).

BCG infections have been reported in health care workers, primarily from exposures resulting from accidental needle sticks or skin lacerations during the preparation of BCG for administration. Nosocomial infections have been reported in patients receiving parenteral drugs that were prepared in areas in which BCG was reconstituted. BCG is capable of dissemination when administered by the intravesical route, and serious infections, including fatal infections, have been reported in patients receiving intravesical BCG (see WARNINGS, PRECAUTIONS, and ADVERSE REACTIONS sections).

DESCRIPTION

TICE® BCG for intravesical use, is an attenuated, live culture preparation of the Bacillus of Calmette and Guerin (BCG) strain of Mycobacterium bovis.^1 The TICE strain was developed at the University of Illinois from a strain originated at the Pasteur Institute.

The medium in which the BCG organism is grown for preparation of the freeze-dried cake is composed of the following ingredients: glycerin, asparagine, citric acid, potassium phosphate, magnesium sulfate, and iron ammonium citrate. The final preparation prior to freeze drying also contains lactose.

The freeze-dried BCG preparation is delivered in glass vials, each containing 1 to 8 × 10^8 colony forming units (CFU) of TICE BCG which is equivalent to approximately 50 mg wet weight. Determination of in vitro potency is achieved through colony counts derived from a serial dilution assay. A single dose consists of 1 reconstituted vial (see DOSAGE AND ADMINISTRATION).

For intravesical use the entire vial is reconstituted with sterile saline. TICE BCG is viable upon reconstitution.

No preservatives have been added.

CLINICAL PHARMACOLOGY

TICE® BCG induces a granulomatous reaction at the local site of administration. Intravesical TICE BCG has been used as a therapy for, and prophylaxis against, recurrent tumors in patients with carcinoma in situ (CIS) of the urinary bladder, and to prevent recurrence of Stage TaT1 papillary tumors of the bladder at high risk of recurrence. The precise mechanism of action is unknown.

CLINICAL STUDIES

Carcinoma in situ (Bladder Cancer)

To evaluate the efficacy of intravesical administration of TICE® BCG in the treatment of carcinoma in situ, patients were identified who had been treated with TICE BCG under 6 different Investigational New Drug (IND) applications in which the most important shared aspect was the use of an induction plus maintenance schedule. Patients received TICE BCG (50 mg; 1 to 8 x 10^8 CFU) intravesically, once weekly for at least 6 weeks and once monthly thereafter for up to 12 months. A longer maintenance was given in some cases.

The study population consisted of 153 patients, 132 males, 19 females, and 2 unidentified as to gender. Thirty patients lacking baseline documentation of CIS and 4 patients lost to follow-up were not evaluable for treatment response. Therefore, 119 patients were available for efficacy evaluation. The mean age was 69 years (range: 38–97 years).

There were 2 categories of clinical response: (1) Complete Histological Response (CR), defined as complete resolution of carcinoma in situ documented by cystoscopy and cytology, with or without biopsy; and (2) Complete Clinical Response Without Cytology (CRNC), defined as an apparent complete disappearance of tumor upon cystoscopy. The results of a 1987 analysis of the evaluable patients are shown in Table 1.

Table 1: The Response of Patients With CIS Bladder Cancer in 6 IND Studies
 | Entered | Evaluable | CR | CRNC | Overall response
No. (%) of patients | 153 | 119 (78%) | 54 (46%) | 36 (30%) | 90 (76%)

A 1989 update of these data is presented in Table 2. The median duration of follow-up was 47 months.

Table 2: Follow-up Response of Patients With CIS Bladder Cancer in 6 IND Studies
1989 Status of 90 Responders (CR or CRNC)
Response | 1987/CR n=54 | 1987/CRNC n=36 | 1987 Response n=90 | Percent
CR | 30 | 15 | 45 | 50
CRNC | 0 | 0 | 0 | 0
Unrelated deaths | 6 | 6 | 12 | 13
Failure | 18 | 15 | 33 | 37

There was no significant difference in response rates between patients with or without prior intravesical chemotherapy. The median duration of response, calculated from the Kaplan-Meier curve as median time to recurrence, is estimated at 4 years or greater. The incidence of cystectomy for 90 patients who achieved a complete response (CR or CRNC) was 11%. The median time to cystectomy in patients who achieved a complete response (CR or CRNC) exceeded 74 months.

TaT1 Bladder Cancer

The efficacy of intravesical TICE BCG in preventing the recurrence of a TaT1 bladder cancer after complete transurethral resection of all papillary tumors was evaluated in 2 open-label, randomized phase III clinical trials. Initial diagnosis of patients included in the studies was determined by cystoscopic biopsies. One was conducted by the Southwestern Oncology Group (SWOG) in patients at high risk of recurrence. High risk was defined as 2 occurrences of tumor within 56 weeks, any stage T1 tumor, or 3 or more tumors presenting simultaneously. The second study was conducted at the Nijmegen University Hospital; Nijmegen, The Netherlands. In this study patients were not selected for high risk of recurrence. In both studies treatment was initiated between 1 and 2 weeks after transurethral resection (TUR).

SWOG Trial (study 8795)

In the SWOG trial (study 8795) patients were randomized to TICE BCG or mitomycin C (MMC). Both drugs were given intravesically weekly for 6 weeks, at 8 and 12 weeks, and then monthly for a total treatment duration of 1 year. Cystoscopy and urinary cytology were performed every 3 months for 2 years. Patients with progressive disease or residual or recurrent disease at or after the 6 month follow-up were removed from the study and were classified as treatment failures.

A total of 469 patients was entered into the study: 237 to the TICE BCG arm and 232 to the MMC arm. Twenty-two patients were subsequently found to be ineligible, and 66 patients had concurrent CIS, and were analyzed separately. Four patients were lost to follow-up, leaving 191 evaluable patients in the TICE BCG arm and 186 in the MMC arm. Of the patients, 84% were male and 16% were female. The average age of these patients was 65 years old.

The Kaplan-Meier estimates of 2-year disease-free survival are shown in Table 3. The difference in disease-free survival time between the 2 groups was statistically significant by the log rank test (P=0.03). The 95% confidence interval of the difference in 2-year disease-free survival was 12% ± 10%. No statistically significant differences between the groups were noted in time to tumor progression, tumor invasion, or overall survival.

Table 3: Results of SWOG Study 8795
 | TICE BCG Arm N=191 | MMC Arm N=186
Estimated disease-free survival at 2 years | 57% | 45%
95% Confidence Interval (CI) | (50%, 65%) | (38%, 53%)

Nijmegen Study

In the Nijmegen study, the efficacy of 3 treatments was compared: TICE substrain BCG, Rijksinstituut voor Volksgezondheid en Milieuhygiene substrain BCG (BCG-RIVM), and MMC.

TICE BCG and BCG-RIVM were given intravesically weekly for 6 weeks. In contrast to the SWOG study, maintenance BCG was not given. Mitomycin C was given intravesically weekly for 4 weeks and then monthly for a total duration of treatment of 6 months. Cystoscopy and urinary cytology were performed every 3 months until recurrence.

A total of 469 patients was enrolled and randomized. Thirty-two patients were not evaluable, 17 were ineligible, 15 were withdrawn before treatment, and 50 had concurrent CIS and were analyzed separately, leaving 387 evaluable patients: 117 in the TICE BCG arm, 134 in the BCG-RIVM arm, and 136 in the MMC arm. Twenty-eight patients (24%) in the TICE BCG arm, 32 patients (24%) in the BCG-RIVM arm, and 24 patients (18%) in the MMC arm had TaG1 tumors. The median duration of follow-up was 22 months (range: 3–54 months).

The Kaplan-Meier estimates of 2-year disease-free survival are shown in Table 4. The differences in disease-free survival among the 3 arms were not statistically significant by the log-rank test (P=0.08).

Table 4: Results of Nijmegen Study
 | TICE BCG Arm N=117 | BCG-RIVM Arm N=134 | MMC Arm N=136
Estimated disease-free survival at 2 years | 53% | 62% | 64%
95% Confidence Interval (CI) | (44%, 64%) | (53%, 72%) | (55%, 74%)

In both the SWOG 8795 study and the Nijmegen study, acute toxicity was more common, and usually more severe, with TICE BCG than with MMC (see ADVERSE REACTIONS).

INDICATIONS AND USAGE

TICE® BCG is indicated for:

- the treatment and prophylaxis of carcinoma in situ (CIS) of the urinary bladder
- the prophylaxis of primary or recurrent stage Ta and/or T1 papillary tumors following transurethral resection (TUR)

Limitations of Use:

- TICE BCG is not recommended for stage TaG1 papillary tumors, unless they are judged to be at high risk of tumor recurrence.
- TICE BCG is not indicated for papillary tumors of stages higher than T1.

CONTRAINDICATIONS

Immunosuppressed Patients

TICE® BCG should not be used in immunosuppressed patients with congenital or acquired immune deficiencies, whether due to concurrent disease (e.g., AIDS, leukemia, lymphoma) cancer therapy (e.g., cytotoxic drugs, radiation), or immunosuppressive therapy (e.g., corticosteroids).

Patients with Increased Risk of BCG Infection

Treatment should be postponed until resolution of a concurrent febrile illness, urinary tract infection, or gross hematuria. Seven to 14 days should elapse before BCG is administered following biopsy, TUR, or traumatic catheterization.

Active Tuberculosis

TICE BCG should not be administered to persons with active tuberculosis. Active tuberculosis should be ruled out in individuals who are PPD positive before starting treatment with TICE BCG.

WARNINGS

BCG LIVE (TICE® BCG) is not a vaccine for the prevention of cancer. BCG Vaccine, not BCG LIVE (TICE BCG), should be used for the prevention of tuberculosis. For vaccination use, refer to BCG Vaccine prescribing information.

Handling Precautions

TICE BCG is an infectious agent. Physicians using this product should be familiar with the literature on the prevention and treatment of BCG-related complications, and should be prepared in such emergencies to contact an infectious disease specialist with experience in treating the infectious complications of intravesical BCG. The treatment of the infectious complications of BCG requires long-term, multiple-drug antibiotic therapy. Special culture media are required for mycobacteria, and physicians administering intravesical BCG or those caring for these patients should have these media readily available.

BCG Infection

Instillation of TICE BCG with an actively bleeding mucosa may promote systemic BCG infection. Treatment should be postponed for at least 1 week following transurethral resection, biopsy, traumatic catheterization, or gross hematuria.

Systemic BCG Reaction

Deaths have been reported as a result of systemic BCG infection and sepsis.^2,3 Patients should be monitored for the presence of symptoms and signs of toxicity after each intravesical treatment. Febrile episodes with flu-like symptoms lasting more than 72 hours, fever ≥103°F, systemic manifestations increasing in intensity with repeated instillations, or persistent abnormalities of liver function tests suggest systemic BCG infection and may require antituberculous therapy. Local symptoms (prostatitis, epididymitis, orchitis) lasting more than 2 to 3 days may also suggest active infection (see WARNINGS, Management of Serious BCG Complications section).

Laboratory Tests

The use of TICE BCG may cause tuberculin sensitivity. Since this is a valuable aid in the diagnosis of tuberculosis, it is advisable to determine the tuberculin reactivity by PPD skin testing before treatment.

Antimicrobial Therapy

Intravesical instillations of BCG should be postponed during treatment with antibiotics, since antimicrobial therapy may interfere with the effectiveness of TICE BCG (see PRECAUTIONS). TICE BCG should not be used in individuals with concurrent infections.

Bladder Capacity

Small bladder capacity has been associated with increased risk of severe local reactions and should be considered in deciding to use TICE BCG therapy.

Management of Serious BCG Complications.

Acute, localized irritative toxicities of TICE BCG may be accompanied by systemic manifestations, consistent with a "flu-like" syndrome. Systemic adverse effects of 1 to 2 days' duration such as malaise, fever, and chills often reflect hypersensitivity reactions. However, symptoms such as fever of ≥38.5°C (101.3°F), or acute localized inflammation such as epididymitis, prostatitis, or orchitis persisting longer than 2 to 3 days suggest active infection, and evaluation for serious infectious complication should be considered.

In patients who develop persistent fever or experience an acute febrile illness consistent with BCG infection, 2 or more antimycobacterial agents should be administered while diagnostic evaluation, including cultures, is conducted. BCG treatment should be discontinued. Negative cultures do not necessarily rule out infection. Physicians using this product should be familiar with the literature on prevention, diagnosis, and treatment of BCG-related complications and, when appropriate, should consult an infectious disease specialist or other physician with experience in the diagnosis and treatment of mycobacterial infections.

TICE BCG is sensitive to the most commonly used antituberculous agents (isoniazid, rifampin, and ethambutol). TICE BCG is not sensitive to pyrazinamide.

PRECAUTIONS

General

TICE® BCG contains live mycobacteria and should be prepared and handled using aseptic technique (see DOSAGE AND ADMINISTRATION, Preparation of Agent section). BCG infections have been reported in health care workers preparing BCG for administration. Needle stick injuries should be avoided during the handling and mixing of TICE BCG. Nosocomial infections have been reported in patients receiving parenteral drugs which were prepared in areas in which BCG was prepared.^4

BCG is capable of dissemination when administered by intravesical route, and serious reactions, including fatal infections, have been reported in patients receiving intravesical BCG.^3 Care should be taken not to traumatize the urinary tract or to introduce contaminants into the urinary system. Seven to 14 days should elapse before TICE BCG is administered following TUR, biopsy, or traumatic catheterization.

TICE BCG should be administered with caution to persons in groups at high risk for HIV infection.

Laboratory Tests

The use of TICE BCG may cause tuberculin sensitivity. It is advisable to determine the tuberculin reactivity of patients receiving TICE BCG by PPD skin testing before treatment is initiated.

Information for Patients

TICE BCG is retained in the bladder for 2 hours and then voided. Patients should void while seated in order to avoid splashing of urine. For the 6 hours after treatment, urine voided should be disinfected for 15 minutes with an equal volume of household bleach before flushing. Patients should be instructed to increase fluid intake in order to "flush" the bladder in the hours following BCG treatment. Patients may experience burning with the first void after treatment.

Patients should be attentive to side effects, such as fever, chills, malaise, flu-like symptoms, or increased fatigue. If the patient experiences severe urinary side effects, such as burning or pain on urination, urgency, frequency of urination, blood in urine, or other symptoms such as joint pain, cough, or skin rash, the physician should be notified.

Drug Interaction

Drug combinations containing immunosuppressants and/or bone marrow depressants and/or radiation interfere with the development of the immune response and should not be used in combination with TICE BCG. Antimicrobial therapy for other infections may interfere with the effectiveness of TICE BCG. There are no data to suggest that the acute, local urinary tract toxicity common with BCG is due to mycobacterial infection, and antituberculosis drugs (e.g., isoniazid) should not be used to prevent or treat the local, irritative toxicities of TICE BCG.

Carcinogenesis, Mutagenesis, Impairment of Fertility

TICE BCG has not been evaluated for its carcinogenic, mutagenic potentials, or impairment of fertility.

Pregnancy

Animal reproduction studies have not been conducted with TICE BCG. It is also not known whether TICE BCG can cause fetal harm when administered to a pregnant woman or can affect reproductive capacity. TICE BCG should not be given to a pregnant woman except when clearly needed. Women should be advised not to become pregnant while on therapy.

Nursing Mothers

It is not known whether TICE BCG is excreted in human milk. Because many drugs are excreted in human milk and because of the potential for serious adverse reactions from TICE BCG in nursing infants, it is advisable to discontinue nursing or to discontinue the drug, taking into account the importance of the drug to the mother.

Pediatric Use

Safety and effectiveness of TICE BCG for the treatment of superficial bladder cancer in pediatric patients have not been established.

Geriatric Use

Of the total number of subjects in clinical studies of TICE BCG, the average age was 66 years old. No overall difference in safety or effectiveness was observed between older and younger subjects. Other reported clinical experience has not identified differences in response between elderly and younger patients, but greater sensitivity of some older individuals to BCG cannot be ruled out.

ADVERSE REACTIONS

Symptoms of bladder irritability, related to the inflammatory response induced, are reported in approximately 60% of patients receiving TICE® BCG. The symptoms typically begin 4 to 6 hours after instillation and last 24 to 72 hours. The irritative side effects are usually seen following the third instillation, and tend to increase in severity after each administration.

The irritative bladder adverse effects can usually be managed symptomatically with products such as pyridium, propantheline bromide, oxybutynin chloride, and acetaminophen. The mechanism of action of the irritative side effects has not been firmly established, but is most consistent with an immunological mechanism.^3 There is no evidence that dose reduction or antituberculous drug therapy can prevent or lessen the irritative toxicity of TICE BCG.

"Flu-like" symptoms (malaise, fever, and chills) which may accompany the localized, irritative toxicities often reflect hypersensitivity reactions which can be treated symptomatically. Antihistamines have also been used.^5

Adverse reactions to TICE BCG tend to be progressive in frequency and severity with subsequent instillation. Delay or postponement of subsequent treatment may or may not reduce the severity of a reaction during subsequent instillation.

Although uncommon, serious infectious complications of intravesical BCG have been reported.^2,3,6 The most serious infectious complication of BCG is disseminated sepsis with associated mortality. In addition, M. bovis infections have been reported in lung, liver, bone, bone marrow, kidney, regional lymph nodes, and prostate in patients who have received intravesical BCG. Systemic infections may be manifested by pneumonitis, hepatitis, cytopenia, vasculitis, infective aneurysm and/or sepsis after a period of fever and malaise during which symptoms progressively increase. Some male genitourinary tract infections (orchitis/epididymitis) have been resistant to multiple-drug antituberculous therapy and required orchiectomy.

If a patient develops persistent fever or experiences an acute febrile illness consistent with BCG infection, BCG treatment should be discontinued and the patient immediately evaluated and treated for systemic infection (see WARNINGS).

The local and systemic adverse reactions reported in a review of 674 patients with superficial bladder cancer, including 153 patients with carcinoma in situ, are summarized in Table 5.

Table 5: Summary of Adverse Effects Seen in 674 Patients With Superficial Bladder Cancer, Including 153 With Carcinoma in Situ
Percent of patients |  |  | Percent of patients
Adverse event | N | Overall (Grade ≥3) | Adverse event | N | Overall (Grade ≥3)
Dysuria | 401 | 60% (11%) | Arthritis/myalgia | 18 | 3% (<1%)
Urinary frequency | 272 | 40% (7%) | Headache/dizziness | 16 | 2%(0)
Flu-like syndrome | 224 | 33% (9%) | Urinary incontinence | 16 | 2% (0)
Hematuria | 175 | 26% (7%) | Anorexia/weight loss | 15 | 2% (<1%)
Fever | 134 | 20% (8%) | Urinary debris | 15 | 2% (<1%)
Malaise/fatigue | 50 | 7% (0) | Allergy | 14 | 2% (<1%)
Cystitis | 40 | 6% (2%) | Cardiac (unclassified) | 13 | 2% (1%)
Urgency | 39 | 6% (1%) | Genital inflammation/
Nocturia | 30 | 5% (1%) | abscess | 12 | 2% (<1%)
Cramps/pain | 27 | 4% (1%) | Respiratory (unclassified) | 11 | 2% (<1%)
Rigors | 22 | 3% (1%) | Urinary tract infection | 10 | 2% (1%)
Nausea/vomiting | 20 | 3% (<1%) | Abdominal pain | 10 | 2% (1%)

The following adverse events were reported in ≤1% of patients: anemia, BCG sepsis, coagulopathy, contracted bladder, diarrhea, epididymitis/prostatitis, hepatic granuloma, hepatitis, leukopenia, neurologic (unclassified), orchitis, pneumonitis, pyuria, rash, thrombocytopenia, urethritis, and urinary obstruction.

In SWOG study 8795, toxicity evaluations were available on a total of 222 TICE BCG-treated patients and 220 MMC-treated patients. Direct bladder toxicity (cramps, dysuria, frequency, urgency, hematuria, hemorrhagic cystitis, or incontinence) was seen more often with TICE BCG with 356 events, compared to 234 events for MMC. Grade ≤2 toxicity was seen significantly more frequently following TICE BCG treatment (P=0.003). No life-threatening toxicity was seen in either arm. Systemic toxicity with TICE BCG was markedly increased compared to that of MMC, with 181 events for TICE BCG compared to 80 for MMC. The frequency of toxicity was increased in all grades, particularly for grades 2 and 3. The most common complaints were malaise, fatigue and lethargy, fever, and abdominal pain. Thirty-two TICE BCG patients were reported to have been treated with isoniazid. Five TICE BCG patients had liver enzyme elevation, including 2 with grade 3 elevations. Eighteen of the 222 (8.1%) TICE BCG patients failed to complete the prescribed protocol compared to 6.2% in the MMC group. Table 6 summarizes the most common adverse reactions reported in this trial.^7

Table 6: Most Common Adverse Reactions in SWOG Study 8795 [The adverse reaction profile of TICE BCG was similar in the Nijmegen study.^8]
 | Study arm
 | TICE BCG (N=222) |  | MMC (N=220)
Adverse event | All Grades | Grade ≥3 | All Grades | Grade ≥3
Dysuria | 115 (52%) | 6 (3%) | 77 (35%) | 5 (2%)
Urgency/frequency | 112 (50%) | 5 (2%) | 63 (29%) | 7 (3%)
Hematuria | 85 (38%) | 6 (3%) | 56 (25%) | 5 (2%)
Flu-like symptoms | 54 (24%) | 1 (<1%) | 29 (13%) | 0
Fever | 37 (17%) | 1 (<1%) | 7 (3%) | 0
Pain (not specified) | 37 (17%) | 4 (2%) | 22 (10%) | 1 (<1%)
Hemorrhagic cystitis | 19 (9%) | 3 (1%) | 10 (5%) | 0
Chills | 19 (9%) | 0 | 2 (1%) | 0
Bladder cramps | 18 (8%) | 0 | 9 (4%) | 0
Nausea | 16 (7%) | 0 | 12 (5%) | 0
Incontinence | 8 (4%) | 0 | 3 (1%) | 0
Myalgia/arthralgia | 7 (3%) | 0 | 0 | 0
Diaphoresis | 7 (3%) | 0 | 1 (<1%) | 0
Rash | 6 (3%) | 1 (<1%) | 16 (7%) | 2 (1%)

Post-marketing Experience

The following adverse reactions have been identified during post-approval use of TICE BCG. Because these reactions are reported voluntarily from a population of uncertain size, it is not always possible to reliably estimate their frequency or establish a causal relationship to drug exposure.

Immune System Disorders: hemophagocytic lymphohistiocytosis (HLH).

OVERDOSAGE

Overdosage occurs if more than 1 vial of TICE® BCG is administered per instillation. If overdosage occurs, the patient should be closely monitored for signs of active local or systemic BCG infection. For acute local or systemic reactions suggesting active infection, an infectious disease specialist experienced in BCG complications should be consulted.

DOSAGE AND ADMINISTRATION

The dose for the intravesical treatment of carcinoma in situ and for the prophylaxis of recurrent papillary tumors consists of 1 vial of TICE® BCG suspended in 50 mL preservative-free saline.

Do not inject subcutaneously or intravenously.

Preparation of Agent

The preparation of the TICE BCG suspension should be done using aseptic technique. To avoid cross-contamination, parenteral drugs should not be prepared in areas where BCG has been prepared. A separate area for the preparation of the TICE BCG suspension is recommended. All equipment, supplies, and receptacles in contact with TICE BCG should be handled and disposed of as biohazardous. The pharmacist or individual responsible for mixing the agent should wear gloves and take precautions to avoid contact of BCG with broken skin. If preparation cannot be performed in a biocontainment hood, then a mask and gown should be worn to avoid inhalation of BCG organisms and inadvertent exposure to broken skin.

Draw 1 mL of sterile, preservative-free saline (0.9% Sodium Chloride Injection USP) at 4–25°C into a small syringe (e.g., 3 mL) and add to 1 vial of TICE BCG to resuspend. Ensure that the needle is inserted through the center of the rubber stopper of the vial. Gently swirl the vial until a homogenous suspension is obtained. Avoid forceful agitation which may cause clumping of the mycobacteria.

Dilute the cloudy TICE BCG suspension in sterile, preservative-free saline to a final volume of 50 mL. Mix the suspension gently prior to intravesical instillation.

The reconstituted TICE BCG should be kept refrigerated (2–8°C), protected from exposure to direct sunlight, and used within 2 hours. Discard unused portion.

Note: DO NOT filter the contents of the TICE BCG vial. Precautions should be taken to avoid exposing the TICE BCG to direct sunlight. Bacteriostatic solutions must be avoided. In addition, use only sterile, preservative-free saline, 0.9% Sodium Chloride Injection USP as diluent.

Treatment and Schedule

Allow 7 to 14 days to elapse after bladder biopsy before TICE BCG is administered. Patients should not drink fluids for 4 hours before treatment and should empty their bladder prior to TICE BCG administration. The reconstituted TICE BCG is instilled into the bladder by gravity flow via the catheter. After instillation of the TICE BCG suspension is complete, remove the catheter. The TICE BCG is retained in the bladder for 2 hours and then voided. Patients unable to retain the suspension for 2 hours should be allowed to void sooner, if necessary.

While the BCG is retained in the bladder, the patient ideally should be repositioned from left side to right side and also should lie upon the back and the abdomen, changing these positions every 15 minutes to maximize bladder surface exposure to the agent.

A standard treatment schedule consists of 1 intravesical instillation per week for 6 weeks. This schedule may be repeated once if tumor remission has not been achieved and if the clinical circumstances warrant. Thereafter, intravesical TICE BCG administration should continue at approximately monthly intervals for at least 6 to 12 months. There are no data to support the interchangeability of BCG LIVE products.

HOW SUPPLIED

TICE® BCG is supplied in a box of 1 single-dose vial of TICE BCG. Each vial contains 1 to 8 × 10^8 CFU, which is equivalent to approximately 50 mg (wet weight), as lyophilized (freeze-dried) powder, NDC 0052-0602-02.

STORAGE

The intact vials of TICE® BCG should be stored refrigerated, at 2–8°C (36–46°F).

This agent contains live bacteria and should be protected from direct sunlight. The product should not be used after the expiration date printed on the label.

REFERENCES

1. DeJager R, Guinan P, Lamm D, Khanna O, Brosman S, DeKernion J, et al. Long-Term Complete Remission in Bladder Carcinoma in Situ with Intravesical TICE Bacillus Calmette Guerin. Urology 1991;38:507–513.
2. Rawls WH, Lamm DL, Lowe BA, Crawford ED, Sarosdy MF, Montie JE, Grossman HB, Scardino PT. Fatal Sepsis Following Intravesical Bacillus Calmette-Guerin Administration For Bladder Cancer. J Urol 1990;144:1328–1330.
3. Lamm DL, van der Meijden APM, Morales A, Brosman SA, Catalona WJ, Herr HW, et al. Incidence and Treatment of Complications of Bacillus Calmette-Guerin Intravesical Therapy in Superficial Bladder Cancer. J. Urol 1992;147:596–600.
4. Stone MM, Vannier AM, Storch SK, Nitta AT, Zhang Y. Brief Report: Meningitis Due to Iatrogenic BCG Infection in Two Immunocompromised Children. NEJM 1995:333:561–563.
5. Steg A, Leleu C, Debre B, Gibod-Boccon L, Sicard D. Systemic Bacillus Calmette-Guerin Infection in Patients Treated by Intravesical BCG Therapy for Superficial Bladder Cancer. EORTC Genitourinary Group Monograph 6: BCG in Superficial Bladder Cancer. Edited by F.M. J. Debruyne, L. Denis and A.P.M. van der Meijden. New York: Alan R. Liss Inc., pp. 325–334.
6. van der Meijden, APM. Practical Approaches to the Prevention and Treatment of Adverse Reactions to BCG. Eur Urol 1995;27(suppl 1):23–28.
7. Lamm DL, Blumenstein BA, Crawford ED, Crissman JD, Lowe BA, Smith JA, Sarosdy MF, Schellhammer PF, Sagalowsky AI, Messing EM, et al. Randomized Intergroup Comparison of Bacillus Calmette-Guerin Immunotherapy and Mitomycin C Chemotherapy Prophylaxis in Superficial Transitional Cell Carcinoma of the Bladder. Urol Oncol 1995;1:119–126.
8. Witjes JA, van der Meijden APM, Witjes WPJ, et al. A Randomized Prospective Study Comparing Intravesical Instillations of Mitomycin-C, BCG-Tice, and BCG-RIVM in pTa-pT1 Tumours and Primary Carcinoma In Situ of the Urinary Bladder. Eur J Cancer 1993;29A(12):1672–1676.

Manufactured for: Merck Sharp & Dohme LLC
Rahway, NJ 07065, USA

Manufactured by: Merck Teknika LLC, Durham, NC 27712, USA

U.S. License No. 1747

For patent information: www.msd.com/research/patent

TICE is a registered trademark of The Board of Trustees of the University of Illinois, used under the license of Merck Teknika LLC, Durham, NC, USA.

Copyright © 2021-2025 Merck & Co., Inc., Rahway, NJ, USA, and its affiliates.
All rights reserved.

Revised: 8/2025

uspi-v914-pwi-2508r012

PRINCIPAL DISPLAY PANEL - 50 mL Vial Carton

NDC 0052-0602-02

BCG
LIVE

(for Intravesical Use)

TICE®
BCG

Rx only

Single-Dose Vial